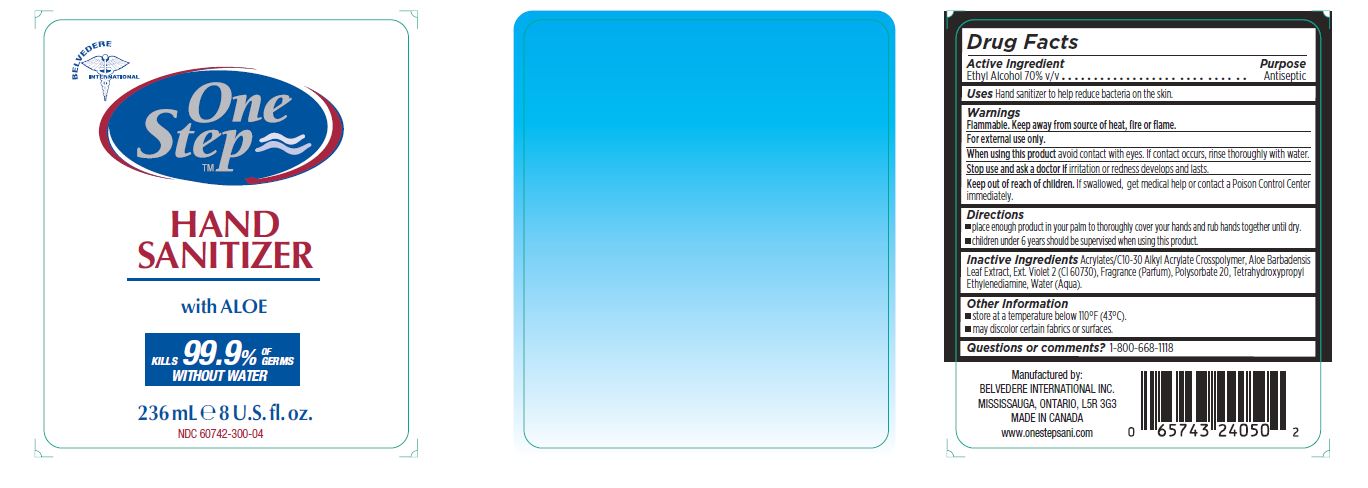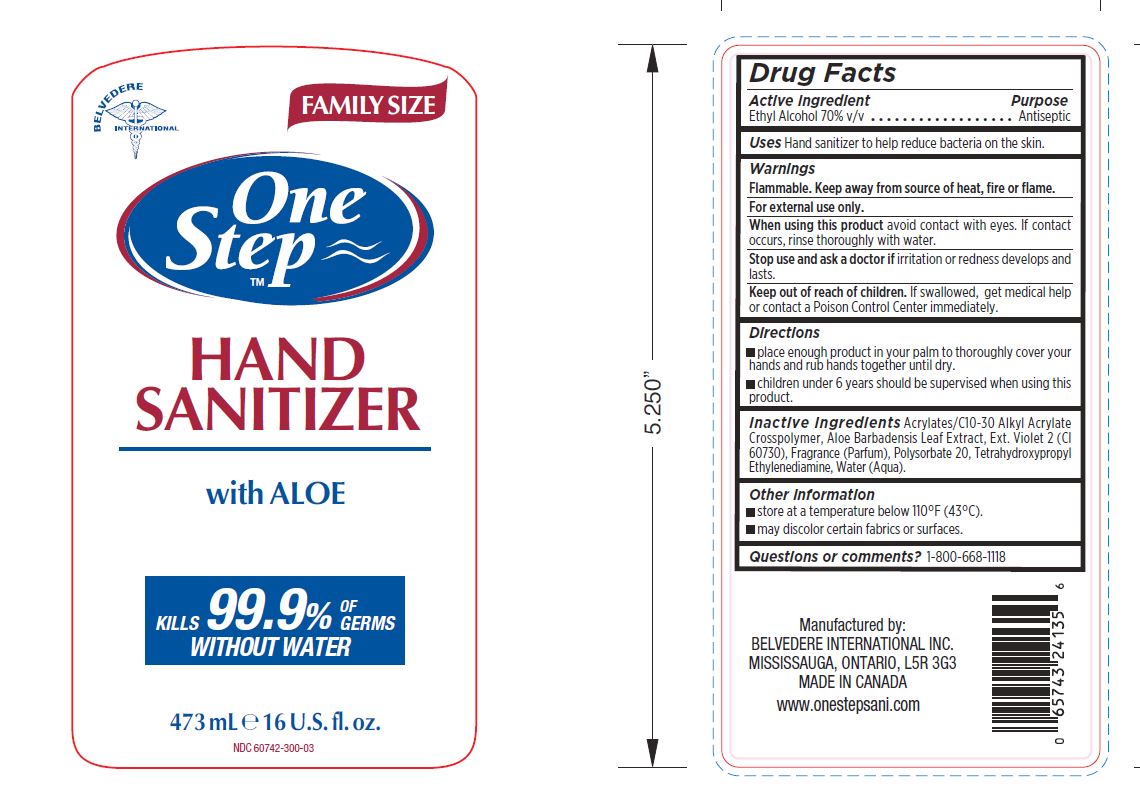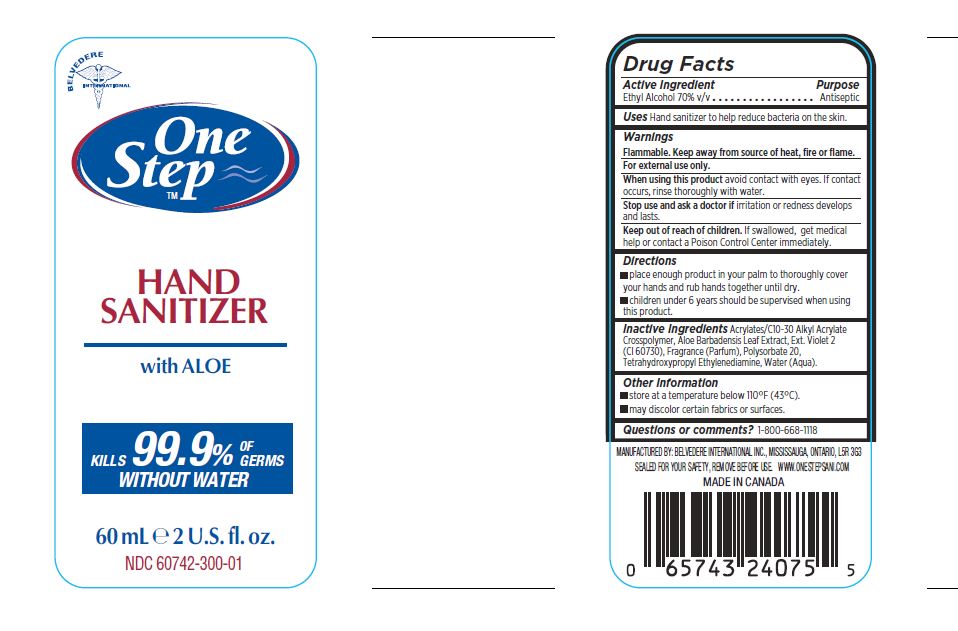 DRUG LABEL: One Step
NDC: 60742-300 | Form: GEL
Manufacturer: Belvedere International Inc.
Category: otc | Type: HUMAN OTC DRUG LABEL
Date: 20190201

ACTIVE INGREDIENTS: ALCOHOL 62 mL/100 mL
INACTIVE INGREDIENTS: WATER; POLYSORBATE 20; EXT. D&C VIOLET NO. 2; CARBOMER HOMOPOLYMER TYPE C; EDETOL; ALOE VERA LEAF

ACTIVE INGREDIENT

Ethyl Alcohol 70% v/v

Uses

Hand Sanitizer to help reduce bacteria on the skin

Keep out of reach of children

Directions

• place enough product in your palm to thoroughly cover your

hands and rub hands together until dry.

• children under 6 years should be supervised when using this

product.

WARNINGS

Flammable. Keep away from source of heat, fire or flame.

For external use only.

When using this product avoid contact with eyes. If contact

occurs, rinse thoroughly with water.

Stop use and ask a doctor if irritation or redness develops and

lasts.

Keep out of reach of children. If swallowed, get medical help

or contact a Poison Control Center immediately.

DOSAGE AND ADMINISTRATION

• place enough product in your palm to thoroughly cover your

hands and rub hands together until dry.

• children under 6 years should be supervised when using this

product.

Inactive Ingredients

Acrylates/C10-30 Alkyl Acrylate Crosspolymer, Aloe Barbadensis Leaf Extract, Ext. Violet 2 (CI 60730), Fragrance (Parfum), Polysorbate 20, Tetrahydroxypropyl Ethylenediamine, Water (Aqua).